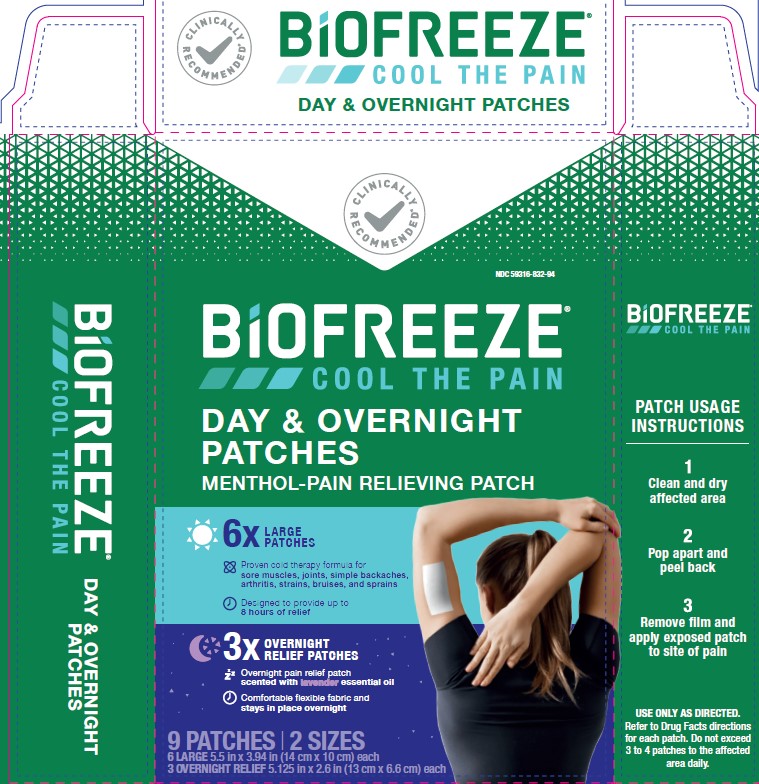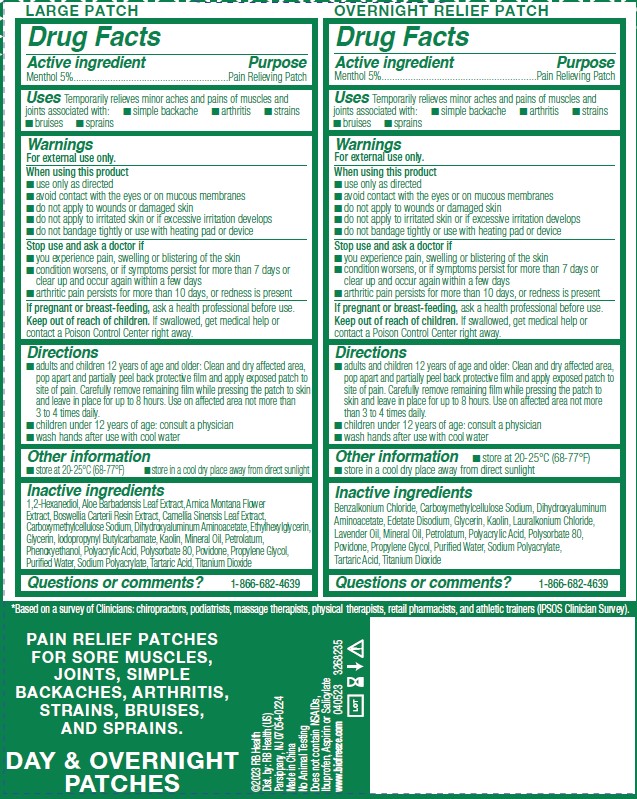 DRUG LABEL: Biofreeze Day and Overnight
NDC: 59316-832 | Form: KIT | Route: TOPICAL
Manufacturer: RB Health (US) LLC
Category: otc | Type: HUMAN OTC DRUG LABEL
Date: 20240404

ACTIVE INGREDIENTS: MENTHOL, UNSPECIFIED FORM 0.3 g/6 g; MENTHOL, UNSPECIFIED FORM 0.05 g/1 g
INACTIVE INGREDIENTS: LAURALKONIUM CHLORIDE; TARTARIC ACID; POLYACRYLIC ACID (450000 MW); CARBOXYMETHYLCELLULOSE SODIUM, UNSPECIFIED; EDETATE DISODIUM; GLYCERIN; MINERAL OIL; POLYSORBATE 80; PROPYLENE GLYCOL; POVIDONE, UNSPECIFIED; TITANIUM DIOXIDE; BENZALKONIUM CHLORIDE; KAOLIN; DIHYDROXYALUMINUM AMINOACETATE; LAVENDER OIL; PETROLATUM; SODIUM POLYACRYLATE (2500000 MW); WATER; WATER; 1,2-HEXANEDIOL; PHENOXYETHANOL; PETROLATUM; GLYCERIN; ARNICA MONTANA FLOWER; MINERAL OIL; POVIDONE, UNSPECIFIED; CARBOXYMETHYLCELLULOSE SODIUM, UNSPECIFIED; ETHYLHEXYLGLYCERIN; GREEN TEA LEAF; IODOPROPYNYL BUTYLCARBAMATE; KAOLIN; FRANKINCENSE; DIHYDROXYALUMINUM AMINOACETATE; PROPYLENE GLYCOL; TARTARIC ACID; TITANIUM DIOXIDE; ALOE VERA LEAF; SODIUM POLYACRYLATE (2500000 MW); POLYACRYLIC ACID (450000 MW); POLYSORBATE 80

Biofreeze Day & Overnight Patches

ACTIVE INGREDIENT

Menthol 5%

Pain Relieving Patch

Uses

Temporarily relieves minor aches and pains of muscles and
joints associated with:

■ simple backache

■ arthritis

■ strains
■ bruises

■ sprains

WARNINGS

For external use only.

When using this product
■ use only as directed
■ avoid contact with the eyes or on mucous membranes
■ do not apply to wounds or damaged skin
■ do not apply to irritated skin or if excessive irritation develops
■ do not bandage tightly or use with heating pad or device

Stop use and ask a doctor if
■ you experience pain, swelling or blistering of the skin
■ condition worsens, or if symptoms persist for more than 7 days or
clear up and occur again within a few days
■ arthritic pain persists for more than 10 days, or redness is present

If pregnant or breast-feeding:

ask a health professional before use.

Keep out of reach of children:

If swallowed, get medical help or contact a Poison Control Center right away

Directions

■ adults and children 12 years of age and older:Clean and dry affected area,

pop apart and partially peel back protective film and apply exposed patch to
site of pain. Carefully remove remaining film while pressing the patch to skin
and leave in place for up to 8 hours. Use on affected area not more than
3 to 4 times daily.

■ children under 12 years of age: consult a physician

■wash hands after use with cool water

Other Information

■ store at 20-25°C (68-77°F)

■ store in a cool dry place away from direct sunlight

INACTIVE INGREDIENT

Large Patch:

1,2-Hexanediol, Aloe Barbadensis Leaf Extract, Arnica Montana Flower
Extract, Boswellia Carterii Resin Extract, Camellia Sinensis Leaf Extract,
Carboxymethylcellulose Sodium, DihydroxyaluminumAminoacetate, Ethylhexylglycerin,
Glycerin, Iodopropynyl Butylcarbamate, Kaolin, Mineral Oil, Petrolatum,
Phenoxyethanol, Polyacrylic Acid, Polysorbate 80, Povidone, Propylene Glycol,
PurifiedWater, Sodium Polyacrylate, Tartaric Acid, Titanium Dioxide

Overnight Relief Patch:

Benzalkonium Chloride, Carboxymethylcellulose Sodium, Dihydroxyaluminum
Aminoacetate, Edetate Disodium, Glycerin, Kaolin, Lauralkonium Chloride,
Lavender Oil, Mineral Oil, Petrolatum, Polyacrylic Acid, Polysorbate 80,
Povidone, Propylene Glycol, Purified Water, Sodium Polyacrylate,
Tartaric Acid, Titanium Dioxide

Questions

1-866-682-4639

Keep out of reach of children.

If swallowed, get medical help or contact a Poison Control Center right away.

PURPOSE

Menthol 5%

Purpose:

Pain Relieving Patch